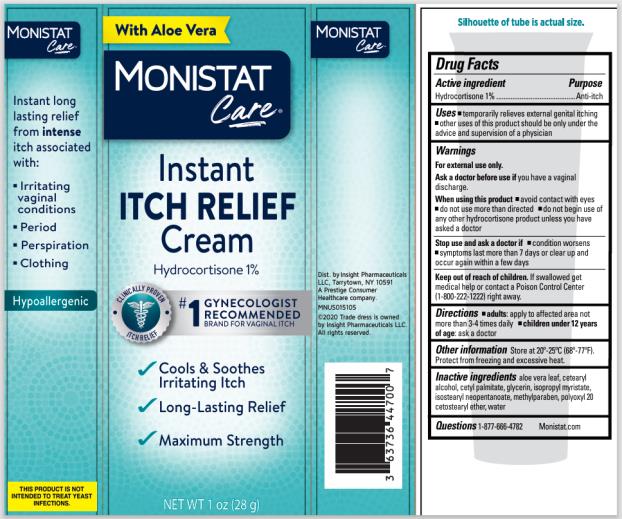 DRUG LABEL: Monistat Complete Care Instant Itch Relief
NDC: 63736-029 | Form: CREAM
Manufacturer: Insight Pharmaceuticals LLC
Category: otc | Type: HUMAN OTC DRUG LABEL
Date: 20241025

ACTIVE INGREDIENTS: HYDROCORTISONE 1 g/100 g
INACTIVE INGREDIENTS: AMMONIUM ACRYLOYLDIMETHYLTAURATE/VP COPOLYMER; CARBOMER HOMOPOLYMER TYPE A; CETEARETH-6; CETYL ALCOHOL; CITRIC ACID MONOHYDRATE; DIMETHICONE; EDETATE DISODIUM; ETHYLPARABEN; GLYCERIN; METHYLPARABEN; MINERAL OIL; PETROLATUM; PHENOXYETHANOL; PROPYLPARABEN; SODIUM CITRATE; SODIUM HYDROXIDE; STEARYL ALCOHOL; WATER; VINYLPYRROLIDONE/EICOSENE COPOLYMER

Monistat Care Itch Relief Cream

Drug Facts

Active Ingredient

Hydrocortisone 1%

Purpose

Anti-itch

Uses

- temporarily relieves external genital itching
- other uses of this product should be only under the advice and supervision of a physician

Warnings

For external use only.

Ask a doctor before use if

you have a vaginal discharge.

When using this product

- avoid contact with eyes
- do not use more than directed
- do not begin use of any other hydrocortisone product unless you have asked a doctor

Stop use and ask a doctor if

- condition worsens
- symptoms last for more than 7 days or clear up and occur again within a few days

Keep out of reach of children.

If swallowed get medical help or contact a Poison Control Center (1-800-222-1222) right away.

Directions

- adults: apply to affected area not more than 3-4 times daily
- children under 12 years of age: ask a doctor

Other Information

- store at 20°-25°C (68°-77°F). Protect from freezing and excessive heat.

Inactive ingredients

aloe vera leaf, cetearyl alcohol, cetyl palmitate, glycerin, isopropyl myristate, isostearyl neopentanoate, methylparaben, polyoxyl 20 cetostearyl ether, water

Questions?

1-877-666-4782 Monistat.com

PRINCIPAL DISPLAY PANEL

MONISTAT Care®

Itch Relief Cream

Hydrocortisone 1%

NEW WT 1 OZ (28 g)